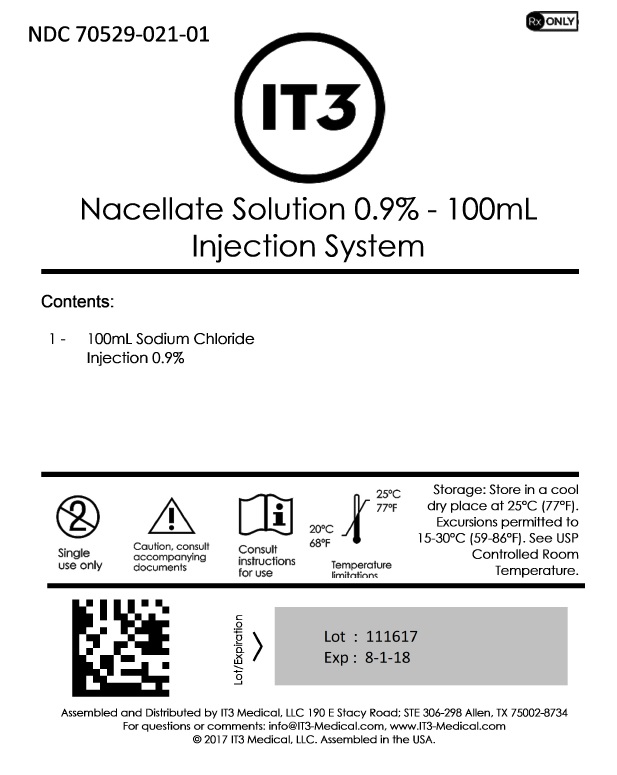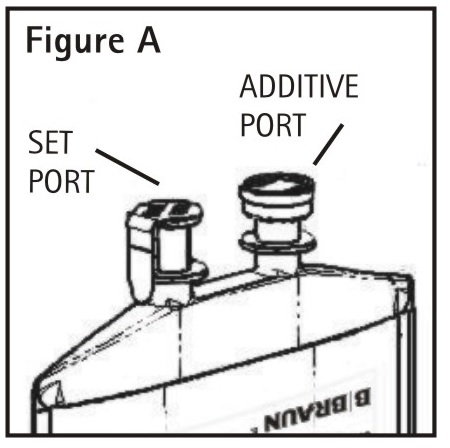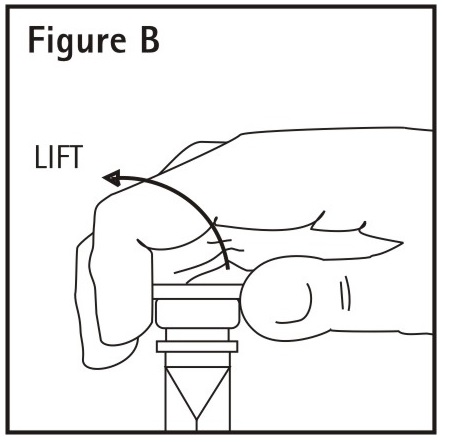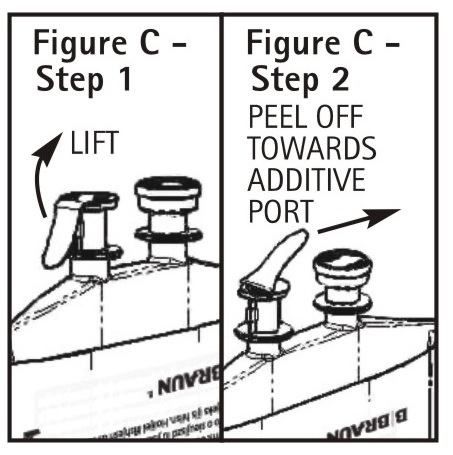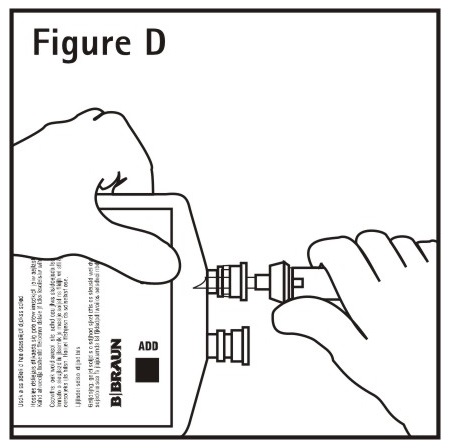 DRUG LABEL: Nacellate Solution 0.9% - 100mL
NDC: 70529-021 | Form: INJECTION, SOLUTION
Manufacturer: IT3 Medical LLC
Category: prescription | Type: HUMAN PRESCRIPTION DRUG LABEL
Date: 20220223

ACTIVE INGREDIENTS: SODIUM CHLORIDE 9 mg/1 mL
INACTIVE INGREDIENTS: WATER; HYDROCHLORIC ACID

Nacellate Solution 0.9% - 100mL

Partial Fill

DESCRIPTION

Each mL of 0.9% Sodium Chloride Injection USP contains:

Sodium Chloride USP 9 mg; Water for Injection USP qs
pH adjusted with Hydrochloric Acid NF
pH: 5.5 (4.5–7.0)
Calculated Osmolarity: 310 mOsmol/liter
Concentration of Electrolytes (mEq/100 mL): Sodium 15.4 Chloride 15.4

This solution is sterile, nonpyrogenic, isotonic and contains no bacteriostatic or antimicrobial agents.

The formula of the active ingredient is:

Ingredient | Molecular Formula | Molecular Weight
Sodium Chloride USP | NaCl | 58.44

Not made with natural rubber latex, PVC or DEHP.

The plastic container is a copolymer of ethylene and propylene formulated and developed for parenteral drugs. The copolymer contains no plasticizers and exhibits virtually no leachability. The safety of the plastic container has been confirmed by biological evaluation procedures. The material passes Class VI testing as specified in the U.S. Pharmacopeia for Biological Tests — Plastic Containers. These tests have shown that the container is nontoxic and biologically inert.

The container/solution unit is a closed system and is not dependent upon entry of external air during administration. The container has two ports, one is for the intravenous administration set and the other is a medication addition site. Each is covered by a tamperproof barrier. Refer to the Directions for Use of the container to properly identify the ports.

No vapor barrier is necessary.

CLINICAL PHARMACOLOGY

0.9% Sodium Chloride Injection USP provides electrolytes and is a source of water for hydration. It is capable of inducing diuresis depending on the clinical condition of the patient.

Sodium, the major cation of the extracellular fluid, functions primarily in the control of water distribution, fluid balance, and osmotic pressure of body fluids. Sodium is also associated with chloride and bicarbonate in the regulation of the acid-base equilibrium of body fluid.

Chloride, the major extracellular anion, closely follows the metabolism of sodium, and changes in the acid-base balance of the body are reflected by changes in the chloride concentration.

INDICATIONS AND USAGE

This intravenous solution is indicated for use in adults and pediatric patients as a source of electrolytes and water for hydration.

This product is designed for use as a diluent and delivery system for intermittent intravenous administration of compatible drug additives. Consult prescribing information for INDICATIONS AND USAGE of drug additives to be administered in this manner.

CONTRAINDICATIONS

This solution is contraindicated where the administration of sodium or chloride could be clinically detrimental.

WARNINGS

Solutions containing sodium ions should be used with great care, if at all, in patients with congestive heart failure, severe renal insufficiency, and in clinical states in which there is sodium retention with edema. In patients with diminished renal function, administration of solutions containing sodium ions may result in sodium retention.

PRECAUTIONS

General

Clinical evaluation and periodic laboratory determinations are necessary to monitor changes in fluid balance, electrolyte concentrations, and acid-base balance during prolonged parenteral therapy or whenever the condition of the patient warrants such evaluation. Significant deviations from normal concentrations may require tailoring of the electrolyte pattern, in this or an alternative solution(s).

Sodium-containing solutions should be administered with caution to patients receiving corticosteroids or corticotropin, or to other salt-retaining patients. Care should be exercised in administering solutions containing sodium to patients with renal or cardiovascular insufficiency, with or without congestive heart failure, particularly if they are postoperative or elderly. See PRECAUTIONS, Geriatric Use.

To minimize the risk of possible incompatibilities arising from mixing this solution with other additives that may be prescribed, the final infusate should be inspected for cloudiness or precipitation immediately after mixing, prior to administration, and periodically during administration.

Laboratory Tests

Periodic laboratory determinations are necessary to monitor changes in fluid balance, electrolyte concentrations, and acid-base balance during prolonged parenteral therapy or whenever the condition of the patient warrants such evaluation.

Drug Interactions

Sodium-containing solutions should be administered with caution to patients receiving cortiscosteroids or corticotrophin.

Some additives may be incompatible. Consult with pharmacist. When introducing additives, use aseptic techniques. Mix thoroughly. Do not store.

Studies have not been conducted to evaluate additional drug/drug or drug/food interactions with Sodium Chloride Injection USP.

Carcinogenesis, Mutagenesis, Impairment of Fertility

Studies with 0.9% Sodium Chloride Injection USP have not been performed to evaluate carcinogenic potential, mutagenic potential or effects on fertility.

Pregnancy

Teratogenic Effects

Pregnancy Category C

Animal reproduction studies have not been conducted with 0.9% Sodium Chloride Injection USP. It is also not known whether 0.9% Sodium Chloride Injection USP can cause fetal harm when administered to a pregnant woman or can affect reproduction capacity. 0.9% Sodium Chloride Injection USP should be given to a pregnant woman only if clearly needed.

Labor and Delivery

Studies have not been conducted to evaluate the effects of Sodium Chloride Injection USP on labor and delivery. As reported in the literature, sodium chloride solutions have been administered during labor and delivery. Caution should be exercised, and the fluid balance, glucose and electrolyte concentrations and acid-base balance, of both mother and fetus should be evaluated periodically or whenever warranted by the condition of the patient or fetus.

Nursing Mothers

Because many drugs are excreted in human milk, caution should be exercised when 0.9% Sodium Chloride Injection USP is administered to a nursing woman.

Pediatric Use

Safety and effectiveness of sodium chloride injections in pediatric patients have not been established by adequate and well controlled trials, however, the use of Sodium Chloride solutions in the pediatric population is referenced in the medical literature. All Warnings, Precautions and Adverse Reactions described in this label apply to pediatric patients.

Geriatric Use

An evaluation of current literature revealed no clinical experience identifying differences in response between elderly and younger patients. In general, dose selection for an elderly patient should be cautious, usually starting at the low end of the dosing range, reflecting the greater frequency of decreased hepatic, renal, or cardiac function, and of concomitant disease or other drug therapy.

This drug is known to be substantially excreted by the kidney, and the risk of toxic reactions may be greater in patients with impaired renal function. Because elderly patients are more likely to have decreased renal function, care should be taken in dose selection, and it may be useful to monitor renal function.

ADVERSE REACTIONS

Reactions which may occur because of the solution or the technique of administration include febrile response, infection at the site of injection, venous thrombosis or phlebitis extending from the site of injection, extravasation, and hypervolemia.

The physician should also be alert to the possibility of adverse reactions to drug additives diluted and administered from the plastic partial fill container. Prescribing information for drug additives to be administered in this manner should be consulted.

Symptoms may result from an excess or deficit of one or more of the ions present in the solution; therefore, frequent monitoring of electrolyte levels is essential.

Hypernatremia may be associated with edema and exacerbation of congestive heart failure due to the retention of water, resulting in an expanded extracellular fluid volume.

If an adverse reaction does occur, discontinue the infusion, evaluate the patient, institute appropriate therapeutic countermeasures, and save the remainder of the fluid for examination if deemed necessary.

OVERDOSAGE

In the event of a fluid or solute overload during parenteral therapy, reevaluate the patient's condition, and institute appropriate corrective treatment.

DOSAGE AND ADMINISTRATION

This solution is for intravenous use only.

Do not use plastic container in series connection.

If administration is controlled by a pumping device, care must be taken to discontinue pumping action before the container runs dry or air embolism may result.

This solution is intended for intravenous administration using sterile equipment. It is recommended that intravenous administration apparatus be replaced at least once every 24 hours.

Use only if solution is clear and container and seals are intact.

As directed by a physician. Dosage is dependent upon the age, weight, and clinical condition of the patient as well as laboratory determinations.

There is no specific pediatric dose. The dose is dependent on weight, clinical condition, and laboratory results. Follow recommendations of appropriate pediatric reference text. See PRECAUTIONS, Pediatric Use.

When using this product as a diluent or vehicle for administration of drug additives, consult the prescribing information of the drug to be used.

Addition of medication should be accomplished using aseptic technique in order to assure sterility.

Physicochemical studies have shown that the container and solution can withstand freezing.

Some additives may be incompatible. Consult with pharmacist. When introducing additives, use aseptic techniques. Mix thoroughly. Do not store.

Parenteral drug products should be inspected visually for particulate matter and discoloration prior to administration, whenever solution and container permit.

HOW SUPPLIED

0.9% Sodium Chloride Injection USP is supplied sterile and nonpyrogenic in partial fill polyolefin containers.

NDC | REF | Fill/Container (mL)
0.9% Sodium Chloride Injection USP
70529-021-01 | S8004-5264 | 100

Exposure of pharmaceutical products to heat should be minimized. Avoid excessive heat. It is recommended that the product be stored at room temperature (25°C); however, brief exposure up to 40°C does not adversely affect the product.

Rx only

Revised: October 2016

Directions For Use of PAB® Container

Partial Additive Bag

Aseptic technique is required.

Caution: Before use, perform the following checks: Read the label. Ensure solution is the one ordered and is within the expiration date.

Inspect the solution in good light for cloudiness, haze or particulate matter; check the container for leakage or damage. Any container which is suspect should not be used.

Use only if solution is clear and container and seals are intact. Single dose container. Discard unused portion. Consult Package Insert for complete product information.

The physician should also be alert to the possibility of adverse reactions to drug additives diluted and administered from the plastic partial fill container. Prescribing information for drug additives to be administered in this manner should be consulted.

Do not use plastic container in series connection.

This solution is intended for intravenous administration using sterile equipment. It is recommended that intravenous administration apparatus be replaced at least once every 24 hours.

Physicochemical studies have shown that the container and solution can withstand freezing.

1. Identify Two Ports (See Figure A).

2. To Add Medication
Remove additive port closure: hold container below additive port and grasp cap between thumb and forefinger then flip cap upward (See Figure B). Swab exposed additive port. Using a syringe with 18 gauge or smaller needle, insert cannula through resealable additive port and add desired drug. Mix thoroughly.
Note: Partial fill bags have been designed to accept an overfill of up to 50 mL.

3. To Attach Administration Set

To aseptically remove the set port closure: hold container below the set port and grasp the foil tab between the thumb and forefinger then pull the tab in two steps as shown in Figure C Steps 1 and 2.

4. Push spike through the diaphragm of the port (See Figure D). Hang container using hole on the lower flap. Prime set in accordance with the Directions for Use provided with the set in use.

When the container is to be used as a diluent and delivery system for intermittent intravenous administration of compatible drug additives, consult prescribing information for INDICATIONS AND USAGE of drug additives to be administered in this manner.

Warning: Some additives may be incompatible. Consult with pharmacist. When introducing additives, use aseptic techniques. Mix thoroughly. Do not store.

PAB® containers can be safely transported in a standard 6-inch carrier through a pneumatic tube system that is well maintained and running properly.

Y36-002-925 LD-224-5

Assembled and Distributed by IT3 Medical, LLC 190 E Stacy Road; STE 306-298, Allen, TX 75002-8734
For questions or comments: info@IT3-Medical.com, www.IT3-Medical.com